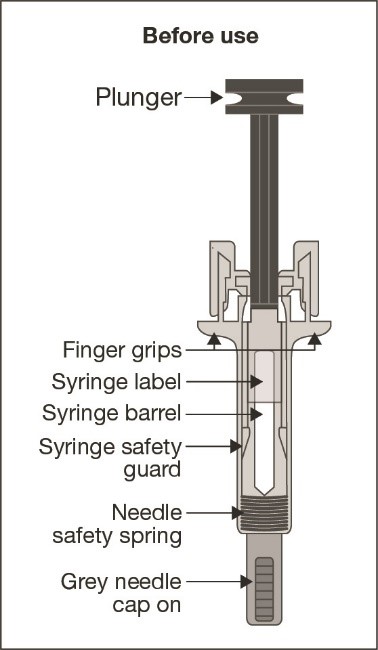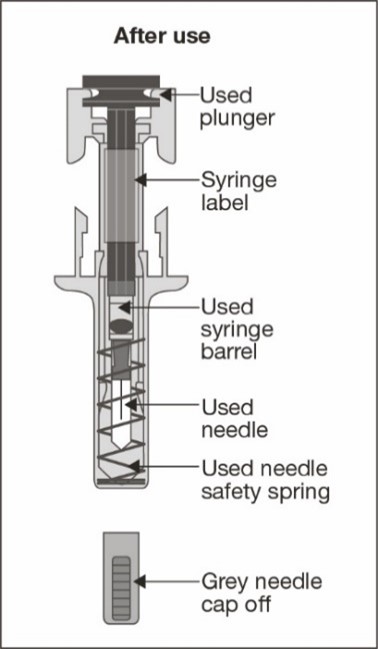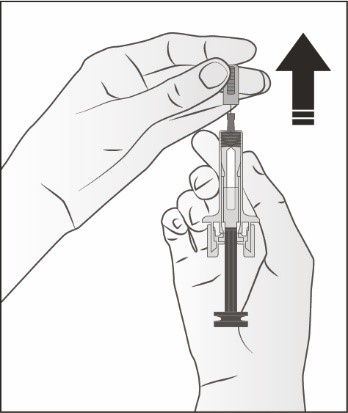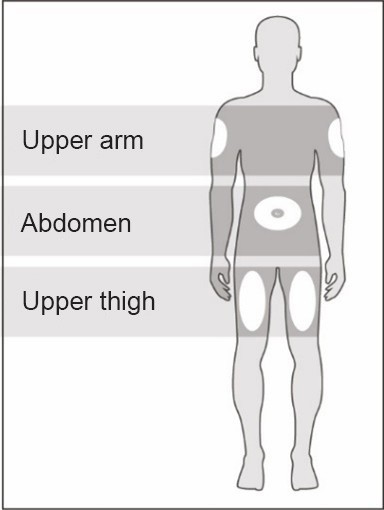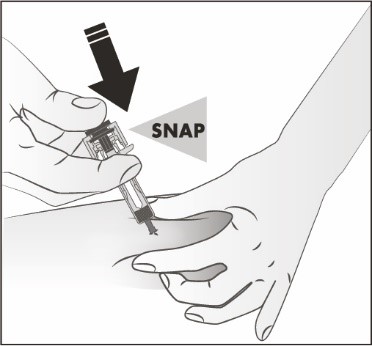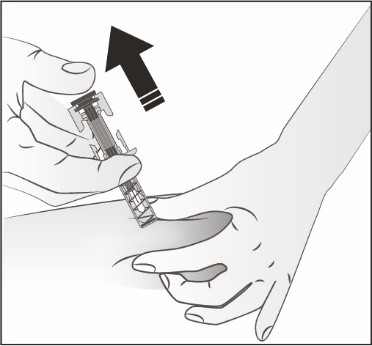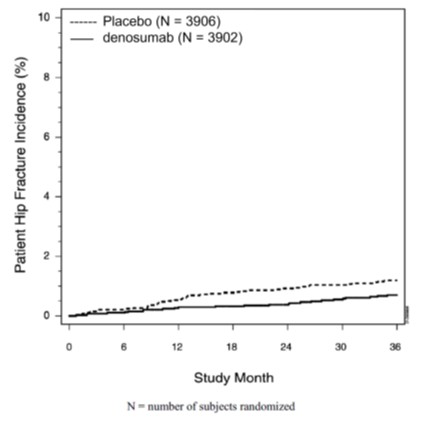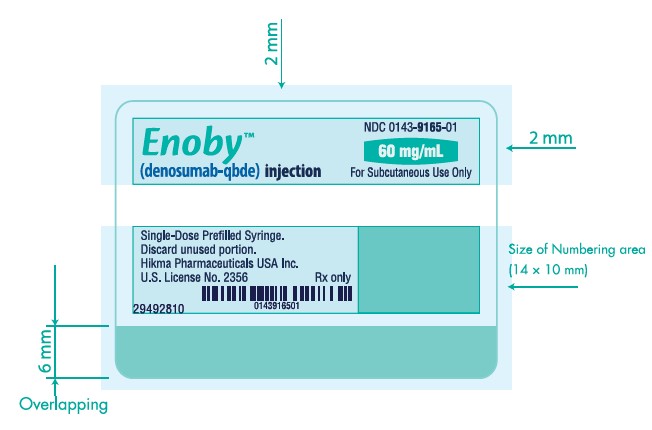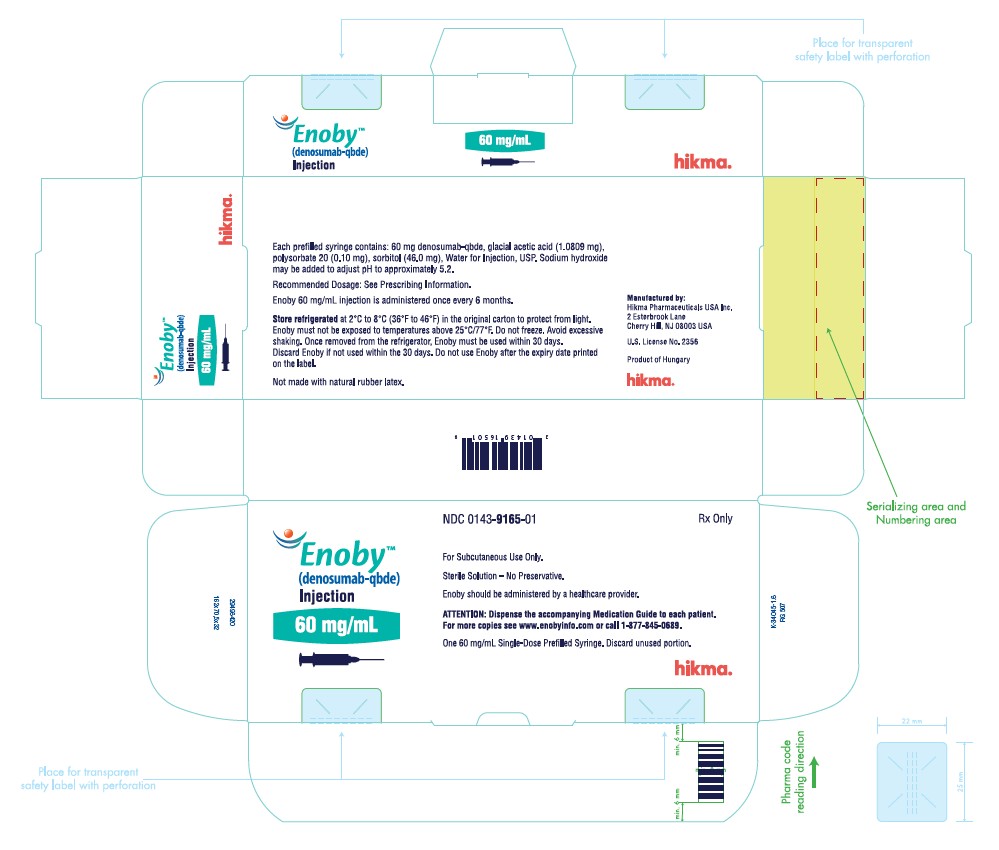 DRUG LABEL: ENOBY
NDC: 0143-9165 | Form: INJECTION
Manufacturer: Hikma Pharmaceuticals USA Inc.
Category: prescription | Type: HUMAN PRESCRIPTION DRUG LABEL
Date: 20260116

ACTIVE INGREDIENTS: DENOSUMAB 60 mg/1 mL
INACTIVE INGREDIENTS: SORBITOL 46 mg/1 mL; SODIUM ACETATE 1.0809  mg/1 mL; POLYSORBATE 20 0.10 mg/1 mL; SODIUM HYDROXIDE; WATER

HIGHLIGHTS OF PRESCRIBING INFORMATION

These highlights do not include all the information needed to use ENOBY™ safely and effectively. See full prescribing information for ENOBY.
ENOBY™ (denosumab-qbde) injection, for subcutaneous use
Initial U.S. Approval: 2025
ENOBY™ (denosumab-qbde) is biosimilar* to PROLIA® (denosumab).

WARNING: SEVERE HYPOCALCEMIA IN PATIENTS WITH ADVANCED KIDNEY DISEASE

See full prescribing information for complete boxed warning.

- Patients with advanced chronic kidney disease are at greater risk of severe hypocalcemia following denosumab products administration. Severe hypocalcemia resulting in hospitalization, life-threatening events and fatal cases have been reported. (5.1)
- The presence of chronic kidney disease-mineral bone disorder (CKD- MBD) markedly increases the risk of hypocalcemia. (5.1)
- Prior to initiating Enoby in patients with advanced chronic kidney disease, evaluate for the presence of CKD-MBD. Treatment with Enoby in these patients should be supervised by a healthcare provider with expertise in the diagnosis and management of CKD-MBD. (2.2, 5.1)

1 INDICATIONS AND USAGE

Enoby is a RANK ligand (RANKL) inhibitor indicated for treatment:

- of postmenopausal women with osteoporosis at high risk for fracture (1.1)
- to increase bone mass in men with osteoporosis at high risk for fracture (1.2)
- of glucocorticoid-induced osteoporosis in men and women at high risk for fracture (1.3)
- to increase bone mass in men at high risk for fracture receiving androgen deprivation therapy for nonmetastatic prostate cancer (1.4)
- to increase bone mass in women at high risk for fracture receiving adjuvant aromatase inhibitor therapy for breast cancer (1.5)

2 DOSAGE AND ADMINISTRATION

- Pregnancy must be ruled out prior to administration of Enoby. (2.1)
- Before initiating Enoby in patients with advanced chronic kidney disease, including dialysis patients, evaluate for the presence of chronic kidney disease mineral and bone disorder with intact parathyroid hormone, serum calcium, 25(OH) vitamin D, and 1,25(OH)2 vitamin D. (2.2, 5.1, 8.6)
- Enoby should be administered by a healthcare provider. (2.3)
- Administer 60 mg every 6 months as a subcutaneous injection in the upper arm, upper thigh, or abdomen. (2.3)
- Instruct patients to take calcium 1000 mg daily and at least 400 IU vitamin D daily. (2.3)

3 DOSAGE FORMS AND STRENGTHS

- Injection: 60 mg/mL solution in a single-dose prefilled syringe (3)

4 CONTRAINDICATIONS

- Hypocalcemia (4, 5.1)
- Pregnancy (4, 8.1)
- Known hypersensitivity to denosumab products (4, 5.3)

5 WARNINGS AND PRECAUTIONS

- Hypocalcemia: Pre-existing hypocalcemia must be corrected before initiating Enoby. May worsen, especially in patients with renal impairment. Adequately supplement all patients with calcium and vitamin D. Concomitant use of calcimimetic drugs may also worsen hypocalcemia risk. Evaluate for presence of chronic kidney disease mineral-bone disorder. Monitor serum calcium. (5.1)
- Same Active Ingredient: Patients receiving Enoby should not receive other denosumab products concomitantly. (5.2)
- Hypersensitivity including anaphylactic reactions may occur. Discontinue permanently if a clinically significant reaction occurs. (5.3)
- Osteonecrosis of the jaw: Has been reported with denosumab products. Monitor for symptoms. (5.4)
- Atypical femoral fractures: Have been reported. Evaluate patients with thigh or groin pain to rule out a femoral fracture. (5.5)
- Multiple vertebral fractures have been reported following treatment discontinuation. Patients should be transitioned to another antiresorptive agent if Enoby is discontinued. (5.6)
- Serious infections including skin infections: May occur, including those leading to hospitalization. Advise patients to seek prompt medical attention if they develop signs or symptoms of infection, including cellulitis. (5.7)
- Dermatologic reactions: Dermatitis, rashes, and eczema have been reported. Consider discontinuing Enoby if severe symptoms develop. (5.8)
- Severe bone, joint, muscle pain may occur. Discontinue use if severe symptoms develop. (5.9)
- Suppression of bone turnover: Significant suppression has been demonstrated. Monitor for consequences of bone over-suppression. (5.10)

6 ADVERSE REACTIONS

- Postmenopausal osteoporosis: Most common adverse reactions (> 5% and more common than placebo) were: back pain, pain in extremity, hypercholesterolemia, musculoskeletal pain, and cystitis. Pancreatitis has been reported in clinical trials. (6.1)
- Male osteoporosis: Most common adverse reactions (> 5% and more common than placebo) were: back pain, arthralgia, and nasopharyngitis. (6.1)
- Glucocorticoid-induced osteoporosis: Most common adverse reactions (> 3% and more common than active-control group) were: back pain, hypertension, bronchitis, and headache. (6.1)
- Bone loss due to hormone ablation for cancer: Most common adverse reactions (≥ 10% and more common than placebo) were: arthralgia and back pain. Pain in extremity and musculoskeletal pain have also been reported in clinical trials. (6.1)

To report SUSPECTED ADVERSE REACTIONS, contact Hikma Pharmaceuticals USA Inc. at 1-877-845-0689 or FDA at 1-800-FDA-1088 or www.fda.gov/medwatch.

8 USE IN SPECIFIC POPULATIONS

- Pregnant women and females of reproductive potential: Denosumab products may cause fetal harm when administered to pregnant women. Advise females of reproductive potential to use effective contraception during therapy, and for at least 5 months after the last dose of Enoby. (8.1, 8.3)
- Pediatric patients: Enoby is not approved for use in pediatric patients. (8.4)
- Renal impairment: No dose adjustment is necessary in patients with renal impairment. Patients with advanced chronic kidney disease (eGFR <30 mL/min/1.73 m^2), including dialysis-dependent patients, are at greater risk of severe hypocalcemia. The presence of underlying chronic kidney disease-mineral bone disorder markedly increases the risk of hypocalcemia. (5.1, 8.6)

*Biosimilar means that the biological product is approved based on data demonstrating that it is highly similar to an FDA-approved biological product, known as a reference product, and that there are no clinically meaningful differences between the biosimilar product and the reference product. Biosimilarity of ENOBY has been demonstrated for the condition(s) of use (e.g., indication(s), dosing regimen(s)), strength(s), dosage form(s), and route(s) of administration described in its Full Prescribing Information.

FULL PRESCRIBING INFORMATION

WARNING: SEVERE HYPOCALCEMIA IN PATIENTS WITH ADVANCED KIDNEY DISEASE

- Patients with advanced chronic kidney disease (eGFR <30 mL/min/1.73 m^2), including dialysis-dependent patients, are at greater risk of severe hypocalcemia following denosumab products administration. Severe hypocalcemia resulting in hospitalization, life-threatening events and fatal cases have been reported [see Warnings and Precautions (5.1)].
- The presence of chronic kidney disease-mineral bone disorder (CKD-MBD) markedly increases the risk of hypocalcemia in these patients [see Warnings and Precautions (5.1)].
- Prior to initiating Enoby in patients with advanced chronic kidney disease, evaluate for the presence of CKD-MBD. Treatment with Enoby in these patients should be supervised by a healthcare provider with expertise in the diagnosis and management of CKD-MBD [see Dosage and Administration (2.2) and Warnings and Precautions (5.1)].

1 INDICATIONS AND USAGE

1.1 Treatment of Postmenopausal Women with Osteoporosis at High Risk for Fracture

Enoby is indicated for the treatment of postmenopausal women with osteoporosis at high risk for fracture, defined as a history of osteoporotic fracture, or multiple risk factors for fracture; or patients who have failed or are intolerant to other available osteoporosis therapy. In postmenopausal women with osteoporosis, denosumab reduces the incidence of vertebral, nonvertebral, and hip fractures [see Clinical Studies (14.1)].

1.2 Treatment to Increase Bone Mass in Men with Osteoporosis

Enoby is indicated for treatment to increase bone mass in men with osteoporosis at high risk for fracture, defined as a history of osteoporotic fracture, or multiple risk factors for fracture; or patients who have failed or are intolerant to other available osteoporosis therapy [see Clinical Studies (14.2)].

1.3 Treatment of Glucocorticoid-Induced Osteoporosis

Enoby is indicated for the treatment of glucocorticoid-induced osteoporosis in men and women at high risk of fracture who are either initiating or continuing systemic glucocorticoids in a daily dosage equivalent to 7.5 mg or greater of prednisone and expected to remain on glucocorticoids for at least 6 months. High risk of fracture is defined as a history of osteoporotic fracture, multiple risk factors for fracture, or patients who have failed or are intolerant to other available osteoporosis therapy [see Clinical Studies (14.3)].

1.4 Treatment of Bone Loss in Men Receiving Androgen Deprivation Therapy for Prostate Cancer

Enoby is indicated as a treatment to increase bone mass in men at high risk for fracture receiving androgen deprivation therapy (ADT) for nonmetastatic prostate cancer. In these patients denosumab also reduced the incidence of vertebral fractures [see Clinical Studies (14.4)].

1.5 Treatment of Bone Loss in Women Receiving Adjuvant Aromatase Inhibitor Therapy for Breast Cancer

Enoby is indicated as a treatment to increase bone mass in women at high risk for fracture receiving adjuvant aromatase inhibitor therapy for breast cancer [see Clinical Studies (14.5)].

2 DOSAGE AND ADMINISTRATION

2.1 Pregnancy Testing Prior to Initiation of Enoby

Pregnancy must be ruled out prior to administration of Enoby. Perform pregnancy testing in all females of reproductive potential prior to administration of Enoby. Based on findings in animals, denosumab products can cause fetal harm when administered to pregnant women [see Use in Specific Populations (8.1, 8.3)].

2.2 Laboratory Testing in Patients with Advanced Chronic Kidney Disease Prior to Initiation of Enoby

In patients with advanced chronic kidney disease [i.e., estimated glomerular filtration rate (eGFR) <30 mL/min/1.73 m^2], including dialysis-dependent patients, evaluate for the presence of chronic kidney disease mineral and bone disorder (CKD-MBD) with intact parathyroid hormone (iPTH), serum calcium, 25(OH) vitamin D, and 1,25 (OH)2 vitamin D prior to decisions regarding Enoby treatment. Consider also assessing bone turnover status (serum markers of bone turnover or bone biopsy) to evaluate the underlying bone disease that may be present [see Warnings and Precautions (5.1)].

2.3 Recommended Dosage

Enoby should be administered by a healthcare provider.

The recommended dose of Enoby is 60 mg administered as a single subcutaneous injection once every 6 months. Administer Enoby via subcutaneous injection in the upper arm, the upper thigh, or the abdomen. All patients should receive calcium 1000 mg daily and at least 400 IU vitamin D daily [see Warnings and Precautions (5.1)].

If a dose of Enoby is missed, administer the injection as soon as the patient is available. Thereafter, schedule injections every 6 months from the date of the last injection.

2.4 Preparation and Administration

Parenteral drug products should be inspected visually for particulate matter and discoloration prior to administration whenever solution and container permit. Enoby is a clear to slightly opalescent, colorless to pale yellow solution. Do not use if the solution is discolored or cloudy or if the solution contains particles or foreign particulate matter.

Prior to administration, Enoby may be removed from the refrigerator and brought to room temperature up to 25°C (77°F) by standing in the original container. This generally takes 15 to 30 minutes. Do not warm Enoby in any other way [see How Supplied/Storage and Handling (16)].

Instructions for Administration of Enoby Prefilled Syringe with Needle Safety Guard

IMPORTANT: In order to minimize accidental needlesticks, the Enoby single-dose prefilled syringe has a clear safety guard that activates automatically to cover the needle after the injection is given.

DO NOT attempt to activate the clear safety guard prior to administering the injection; it will lock in place and prevent injection.

Step 1: Remove Gray Needle Cap (Figure A)

Figure A

Step 2: Administer Subcutaneous Injection

- Choose an injection site (Figure B).

The recommended injection sites for Enoby include:

- the upper arm OR
- the upper thigh OR
- the abdomen.

Do not press the plunger while inserting the needle.

Figure B

Do not administer into muscle or blood vessel.

- Pinch the skin and insert at a 45 to 90-degree angle. Push the plunger with slow and constant pressure all the way down until you feel or hear a “snap” (Figure C).

Figure C

Step 3: Release Plunger and Dispose of Syringe

- Keeping the prefilled syringe at the injection site, release the thumb from the plunger and lift syringe.
- The syringe safety guard will automatically cover the injection needle (Figure D).

Figure D

- Immediately dispose of the syringe and needle cap in the nearest sharps container.

Do not put the needle cap back on the used syringe.

3 DOSAGE FORMS AND STRENGTHS

- Injection: 60 mg/mL clear to slightly opalescent, colorless to pale yellow solution in a single-dose prefilled syringe.

4 CONTRAINDICATIONS

Enoby is contraindicated in:

- Patients with hypocalcemia: Pre-existing hypocalcemia must be corrected prior to initiating therapy with Enoby [see Warnings and Precautions (5.1)].
- Pregnant women: Denosumab products may cause fetal harm when administered to a pregnant woman. In women of reproductive potential, pregnancy testing should be performed prior to initiating treatment with Enoby [see Use in Specific Populations (8.1)].
- Patients with hypersensitivity to denosumab products: Enoby is contraindicated in patients with a history of systemic hypersensitivity to any component of the product. Reactions have included anaphylaxis, facial swelling, and urticaria [see Warnings and Precautions (5.3), Adverse Reactions (6.2)].

5 WARNINGS AND PRECAUTIONS

5.1 Severe Hypocalcemia and Mineral Metabolism Changes

Denosumab products can cause severe hypocalcemia and fatal cases have been reported. Pre-existing hypocalcemia must be corrected prior to initiating therapy with Enoby. Adequately supplement all patients with calcium and vitamin D [see Dosage and Administration (2.1), Contraindications (4), and Adverse Reactions (6.1)].

In patients without advanced chronic kidney disease who are predisposed to hypocalcemia and disturbances of mineral metabolism (e.g., history of hypoparathyroidism, thyroid surgery, parathyroid surgery, malabsorption syndromes, excision of small intestine, treatment with other calcium-lowering drugs), assess serum calcium and mineral levels (phosphorus and magnesium) 10 to 14 days after Enoby injection. In some postmarketing cases, hypocalcemia persisted for weeks or months and required frequent monitoring and intravenous and/or oral calcium replacement, with or without vitamin D.

Patients with Advanced Chronic Kidney Disease

Patients with advanced chronic kidney disease [i.e., eGFR < 30 mL/min/1.73 m^2] including dialysis-dependent patients are at greater risk for severe hypocalcemia following denosumab products administration. Severe hypocalcemia resulting in hospitalization, life-threatening events and fatal cases have been reported. The presence of underlying chronic kidney disease-mineral bone disorder (CKD-MBD, renal osteodystrophy) markedly increases the risk of hypocalcemia. Concomitant use of calcimimetic drugs may also worsen hypocalcemia risk.

To minimize the risk of hypocalcemia in patients with advanced chronic kidney disease, evaluate for the presence of chronic kidney disease mineral and bone disorder with intact parathyroid hormone (iPTH), serum calcium, 25(OH) vitamin D, and 1,25(OH)2 vitamin D prior to decisions regarding Enoby treatment. Consider also assessing bone turnover status (serum markers of bone turnover or bone biopsy) to evaluate the underlying bone disease that may be present. Monitor serum calcium weekly for the first month after Enoby administration and monthly thereafter. Instruct all patients with advanced chronic kidney disease, including those who are dialysis-dependent, about the symptoms of hypocalcemia and the importance of maintaining serum calcium levels with adequate calcium and activated vitamin D supplementation. Treatment with Enoby in these patients should be supervised by a healthcare provider who is experienced in diagnosis and management of CKD-MBD.

5.2 Drug Products with Same Active Ingredient

Patients receiving Enoby should not receive other denosumab products concomitantly.

5.3 Hypersensitivity

Clinically significant hypersensitivity including anaphylaxis has been reported with denosumab products. Symptoms have included hypotension, dyspnea, throat tightness, facial and upper airway edema, pruritus, and urticaria. If an anaphylactic or other clinically significant allergic reaction occurs, initiate appropriate therapy and discontinue further use of Enoby [see Contraindications (4), Adverse Reactions (6.2)].

5.4 Osteonecrosis of the Jaw

Osteonecrosis of the jaw (ONJ), which can occur spontaneously, is generally associated with tooth extraction and/or local infection with delayed healing. ONJ has been reported in patients receiving denosumab products [see Adverse Reactions (6.1)]. A routine oral exam should be performed by the prescriber prior to initiation of Enoby treatment. A dental examination with appropriate preventive dentistry is recommended prior to treatment with Enoby in patients with risk factors for ONJ such as invasive dental procedures (e.g., tooth extraction, dental implants, oral surgery), diagnosis of cancer, concomitant therapies (e.g., chemotherapy, corticosteroids, angiogenesis inhibitors), poor oral hygiene, and comorbid disorders (e.g., periodontal and/or other pre-existing dental disease, anemia, coagulopathy, infection, ill-fitting dentures). Good oral hygiene practices should be maintained during treatment with Enoby. Concomitant administration of drugs associated with ONJ may increase the risk of developing ONJ. The risk of ONJ may increase with duration of exposure to denosumab products.

For patients requiring invasive dental procedures, clinical judgment of the treating physician and/or oral surgeon should guide the management plan of each patient based on individual benefit-risk assessment.

Patients who are suspected of having or who develop ONJ while on Enoby should receive care by a dentist or an oral surgeon. In these patients, extensive dental surgery to treat ONJ may exacerbate the condition. Discontinuation of Enoby therapy should be considered based on individual benefit-risk assessment.

5.5 Atypical Subtrochanteric and Diaphyseal Femoral Fractures

Atypical low energy or low trauma fractures of the shaft have been reported in patients receiving denosumab products [see Adverse Reactions (6.1)]. These fractures can occur anywhere in the femoral shaft from just below the lesser trochanter to above the supracondylar flare and are transverse or short oblique in orientation without evidence of comminution. Causality has not been established as these fractures also occur in osteoporotic patients who have not been treated with antiresorptive agents.

Atypical femoral fractures most commonly occur with minimal or no trauma to the affected area. They may be bilateral, and many patients report prodromal pain in the affected area, usually presenting as dull, aching thigh pain, weeks to months before a complete fracture occurs. A number of reports note that patients were also receiving treatment with glucocorticoids (e.g. prednisone) at the time of fracture.

During Enoby treatment, patients should be advised to report new or unusual thigh, hip, or groin pain. Any patient who presents with thigh or groin pain should be suspected of having an atypical fracture and should be evaluated to rule out an incomplete femur fracture. Patients presenting with an atypical femur fracture should also be assessed for symptoms and signs of fracture in the contralateral limb. Interruption of Enoby therapy should be considered, pending a benefit-risk assessment, on an individual basis.

5.6 Multiple Vertebral Fractures (MVF) Following Treatment Discontinuation

Following discontinuation of denosumab treatment, fracture risk increases, including the risk of multiple vertebral fractures. Treatment with denosumab results in significant suppression of bone turnover and cessation of denosumab treatment results in increased bone turnover above pretreatment values 9 months after the last dose of denosumab. Bone turnover then returns to pretreatment values 24 months after the last dose of denosumab. In addition, bone mineral density (BMD) returns to pretreatment values within 18 months after the last injection [see Clinical Pharmacology (12.2), Clinical Studies (14.1)].

New vertebral fractures occurred as early as 7 months (on average 19 months) after the last dose of denosumab. Prior vertebral fracture was a predictor of multiple vertebral fractures after denosumab discontinuation. Evaluate an individual’s benefit-risk before initiating treatment with Enoby.

If Enoby treatment is discontinued, patients should be transitioned to an alternative antiresorptive therapy [see Adverse Reactions (6.1)].

5.7 Serious Infections

In a clinical trial of over 7800 women with postmenopausal osteoporosis, serious infections leading to hospitalization were reported more frequently in the denosumab group than in the placebo group [see Adverse Reactions (6.1)]. Serious skin infections, as well as infections of the abdomen, urinary tract, and ear, were more frequent in patients treated with denosumab. Endocarditis was also reported more frequently in denosumab-treated patients. The incidence of opportunistic infections was similar between placebo and denosumab groups, and the overall incidence of infections was similar between the treatment groups. Advise patients to seek prompt medical attention if they develop signs or symptoms of severe infection, including cellulitis.

Patients on concomitant immunosuppressant agents or with impaired immune systems may be at increased risk for serious infections. Consider the benefit-risk profile in such patients before treating with Enoby. In patients who develop serious infections while on Enoby, prescribers should assess the need for continued Enoby therapy.

5.8 Dermatologic Adverse Reactions

In a large clinical trial of over 7800 women with postmenopausal osteoporosis, epidermal and dermal adverse events such as dermatitis, eczema, and rashes occurred at a significantly higher rate in the denosumab group compared to the placebo group. Most of these events were not specific to the injection site [see Adverse Reactions (6.1)]. Consider discontinuing Enoby if severe symptoms develop.

5.9 Musculoskeletal Pain

In postmarketing experience, severe and occasionally incapacitating bone, joint, and/or muscle pain has been reported in patients taking denosumab products [see Adverse Reactions (6.2)]. The time to onset of symptoms varied from one day to several months after starting denosumab products. Consider discontinuing use if severe symptoms develop [see Patient Counseling Information (17)].

5.10 Suppression of Bone Turnover

In clinical trials in women with postmenopausal osteoporosis, treatment with denosumab resulted in significant suppression of bone remodeling as evidenced by markers of bone turnover and bone histomorphometry [see Clinical Pharmacology (12.2), Clinical Studies (14.1)]. The significance of these findings and the effect of long-term treatment with denosumab products are unknown. The long-term consequences of the degree of suppression of bone remodeling observed with denosumab may contribute to adverse outcomes such as osteonecrosis of the jaw, atypical fractures, and delayed fracture healing. Monitor patients for these consequences.

5.11 Hypercalcemia in Pediatric Patients with Osteogenesis Imperfecta

Enoby is not approved for use in pediatric patients. Hypercalcemia has been reported in pediatric patients with osteogenesis imperfecta treated with denosumab products. Some cases required hospitalization [see Use in Specific Populations (8.4)].

6 ADVERSE REACTIONS

The following serious adverse reactions are discussed below and also elsewhere in the labeling:

- Severe Hypocalcemia and Mineral Metabolism Changes [see Warnings and Precautions (5.1)]
- Hypersensitivity [see Warnings and Precautions (5.3)]
- Osteonecrosis of the Jaw [see Warnings and Precautions (5.4)]
- Atypical Subtrochanteric and Diaphyseal Femoral Fractures [see Warnings and Precautions (5.5)]
- Multiple Vertebral Fractures (MVF) Following Treatment Discontinuation [see Warnings and Precautions (5.6)]
- Serious Infections [see Warnings and Precautions (5.7)]
- Dermatologic Adverse Reactions [see Warnings and Precautions (5.8)]

The most common adverse reactions reported with denosumab products in patients with postmenopausal osteoporosis are back pain, pain in extremity, musculoskeletal pain, hypercholesterolemia, and cystitis.

The most common adverse reactions reported with denosumab products in men with osteoporosis are back pain, arthralgia, and nasopharyngitis.

The most common adverse reactions reported with denosumab products in patients with glucocorticoid-induced osteoporosis are back pain, hypertension, bronchitis, and headache.

The most common (per patient incidence ≥ 10%) adverse reactions reported with denosumab products in patients with bone loss receiving androgen deprivation therapy for prostate cancer or adjuvant aromatase inhibitor therapy for breast cancer are arthralgia and back pain. Pain in extremity and musculoskeletal pain have also been reported in clinical trials.

The most common adverse reactions leading to discontinuation of denosumab products in patients with postmenopausal osteoporosis are back pain and constipation.

6.1 Clinical Trials Experience

Because clinical studies are conducted under widely varying conditions, adverse reaction rates observed in the clinical studies of a drug cannot be directly compared to rates in the clinical studies of another drug and may not reflect the rates observed in clinical practice.

Treatment of Postmenopausal Women with Osteoporosis

The safety of denosumab in the treatment of postmenopausal osteoporosis was assessed in a 3-year, randomized, double-blind, placebo-controlled, multinational study of 7808 postmenopausal women aged 60 to 91 years. A total of 3876 women were exposed to placebo and 3886 women were exposed to denosumab administered subcutaneously once every 6 months as a single 60 mg dose. All women were instructed to take at least 1000 mg of calcium and 400 IU of vitamin D supplementation per day.

The incidence of all-cause mortality was 2.3% (n = 90) in the placebo group and 1.8% (n = 70) in the denosumab group. The incidence of nonfatal serious adverse events was 24.2% in the placebo group and 25.0% in the denosumab group. The percentage of patients who withdrew from the study due to adverse events was 2.1% and 2.4% for the placebo and denosumab groups, respectively. The most common adverse reactions reported with denosumab in patients with postmenopausal osteoporosis are back pain, pain in extremity, musculoskeletal pain, hypercholesterolemia, and cystitis.

Adverse reactions reported in ≥ 2% of postmenopausal women with osteoporosis and more frequently in the denosumab-treated women than in the placebo-treated women are shown in the table below.

Table 1. Adverse Reactions Occurring in ≥ 2% of Patients with Osteoporosis and More Frequently than in Placebo-treated Patients

Preferred Term | Denosumab; (N = 3886); n (%) | Placebo; (N = 3876); n (%)
Back pain | 1347 (34.7) | 1340 (34.6)
Pain in extremity | 453 (11.7) | 430 (11.1)
Musculoskeletal pain | 297 (7.6) | 291 (7.5)
Hypercholesterolemia | 280 (7.2) | 236 (6.1)
Cystitis | 228 (5.9) | 225 (5.8)
Vertigo | 195 (5.0) | 187 (4.8)
Upper respiratory tract infection | 190 (4.9) | 167 (4.3)
Edema peripheral | 189 (4.9) | 155 (4.0)
Sciatica | 178 (4.6) | 149 (3.8)
Bone pain | 142 (3.7) | 117 (3.0)
Abdominal pain upper | 129 (3.3) | 111 (2.9)
Anemia | 129 (3.3) | 107 (2.8)
Insomnia | 126 (3.2) | 122 (3.1)
Myalgia | 114 (2.9) | 94 (2.4)
Angina pectoris | 101 (2.6) | 87 (2.2)
Rash | 96 (2.5) | 79 (2.0)
Pharyngitis | 91 (2.3) | 78 (2.0)
Asthenia | 90 (2.3) | 73 (1.9)
Pruritus | 87 (2.2) | 82 (2.1)
Flatulence | 84 (2.2) | 53 (1.4)
Spinal osteoarthritis | 82 (2.1) | 64 (1.7)
Gastroesophageal reflux disease | 80 (2.1) | 66 (1.7)
Herpes zoster | 79 (2.0) | 72 (1.9)

Hypocalcemia

Decreases in serum calcium levels to less than 8.5 mg/dL at any visit were reported in 0.4% women in the placebo group and 1.7% women in the denosumab group. The nadir in serum calcium level occurred at approximately day 10 after denosumab dosing in subjects with normal renal function.

In clinical studies, subjects with impaired renal function were more likely to have greater reductions in serum calcium levels compared to subjects with normal renal function. In a study of 55 subjects with varying degrees of renal function, serum calcium levels < 7.5 mg/dL or symptomatic hypocalcemia were observed in 5 subjects. These included no subjects in the normal renal function group, 10% of subjects in the creatinine clearance 50 to 80 mL/min group, 29% of subjects in the creatinine clearance < 30 mL/min group, and 29% of subjects in the hemodialysis group. These subjects did not receive calcium and vitamin D supplementation. In a study of 4550 postmenopausal women with osteoporosis, the mean change from baseline in serum calcium level 10 days after denosumab dosing was -5.5% in subjects with creatinine clearance < 30 mL/min vs. -3.1% in subjects with creatinine clearance ≥ 30 mL/min.

Serious Infections

Receptor activator of nuclear factor kappa-B ligand (RANKL) is expressed on activated T and B lymphocytes and in lymph nodes. Therefore, a RANKL inhibitor such as denosumab products may increase the risk of infection.

In the clinical study of 7808 postmenopausal women with osteoporosis, the incidence of infections resulting in death was 0.2% in both placebo and denosumab treatment groups. However, the incidence of nonfatal serious infections was 3.3% in the placebo and 4.0% in the denosumab groups. Hospitalizations due to serious infections in the abdomen (0.7% placebo vs. 0.9% denosumab), urinary tract (0.5% placebo vs. 0.7% denosumab), and ear (0.0% placebo vs. 0.1% denosumab) were reported. Endocarditis was reported in no placebo patients and 3 patients receiving denosumab.

Skin infections, including erysipelas and cellulitis, leading to hospitalization were reported more frequently in patients treated with denosumab (< 0.1% placebo vs. 0.4% denosumab).

The incidence of opportunistic infections was similar to that reported with placebo.

Dermatologic Adverse Reactions

A significantly higher number of patients treated with denosumab developed epidermal and dermal adverse events (such as dermatitis, eczema, and rashes), with these events reported in 8.2% of the placebo and 10.8% of the denosumab groups (p < 0.0001). Most of these events were not specific to the injection site [see Warnings and Precautions (5.8)].

Osteonecrosis of the Jaw

ONJ has been reported in the osteoporosis clinical trial program in patients treated with denosumab [see Warnings and Precautions (5.4)].

Atypical Subtrochanteric and Diaphyseal Femoral Fractures

In the osteoporosis clinical trial program, atypical femoral fractures were reported in patients treated with denosumab. The duration of denosumab exposure to time of atypical femoral fracture diagnosis was as early as 2 1/2; years [see Warnings and Precautions (5.5)].

Multiple Vertebral Fractures (MVF) Following Treatment Discontinuation

In the osteoporosis clinical trial program, multiple vertebral fractures were reported in patients after discontinuation of denosumab. In the phase 3 trial in women with postmenopausal osteoporosis, 6% of women who discontinued denosumab and remained in the study developed new vertebral fractures, and 3% of women who discontinued denosumab and remained in the study developed multiple new vertebral fractures. The mean time to onset of multiple vertebral fractures was 17 months (range: 7-43 months) after the last injection of denosumab. Prior vertebral fracture was a predictor of multiple vertebral fractures after discontinuation [see Warnings and Precautions (5.6)].

Pancreatitis

Pancreatitis was reported in 4 patients (0.1%) in the placebo and 8 patients (0.2%) in the denosumab groups. Of these reports, 1 patient in the placebo group and all 8 patients in the denosumab group had serious events, including one death in the denosumab group. Several patients had a prior history of pancreatitis. The time from product administration to event occurrence was variable.

New Malignancies

The overall incidence of new malignancies was 4.3% in the placebo and 4.8% in the denosumab groups. New malignancies related to the breast (0.7% placebo vs. 0.9% denosumab), reproductive system (0.2% placebo vs. 0.5% denosumab), and gastrointestinal system (0.6% placebo vs. 0.9% denosumab) were reported. A causal relationship to drug exposure has not been established.

Treatment to Increase Bone Mass in Men with Osteoporosis

The safety of denosumab in the treatment of men with osteoporosis was assessed in a 1-year randomized, double-blind, placebo-controlled study. A total of 120 men were exposed to placebo and 120 men were exposed to denosumab administered subcutaneously once every 6 months as a single 60 mg dose. All men were instructed to take at least 1000 mg of calcium and 800 IU of vitamin D supplementation per day.

The incidence of all-cause mortality was 0.8% (n = 1) in the placebo group and 0.8% (n = 1) in the denosumab group. The incidence of nonfatal serious adverse events was 7.5% in the placebo group and 8.3% in the denosumab group. The percentage of patients who withdrew from the study due to adverse events was 0% and 2.5% for the placebo and denosumab groups, respectively.

Adverse reactions reported in ≥ 5% of men with osteoporosis and more frequently with denosumab than in the placebo-treated patients were: back pain (6.7% placebo vs. 8.3% denosumab), arthralgia (5.8% placebo vs. 6.7% denosumab), and nasopharyngitis (5.8% placebo vs. 6.7% denosumab).

Serious Infections

Serious infection was reported in 1 patient (0.8%) in the placebo group and no patients in the denosumab group.

Dermatologic Adverse Reactions

Epidermal and dermal adverse events (such as dermatitis, eczema, and rashes) were reported in 4 patients (3.3%) in the placebo group and 5 patients (4.2%) in the denosumab group.

Osteonecrosis of the Jaw

No cases of ONJ were reported.

Pancreatitis

Pancreatitis was reported in 1 patient (0.8%) in the placebo group and 1 patient (0.8%) in the denosumab group.

New Malignancies

New malignancies were reported in no patients in the placebo group and 4 (3.3%) patients (3 prostate cancers, 1 basal cell carcinoma) in the denosumab group.

Treatment of Glucocorticoid-Induced Osteoporosis

The safety of denosumab in the treatment of glucocorticoid-induced osteoporosis was assessed in the 1-year, primary analysis of a 2-year randomized, multicenter, double-blind, parallel-group, active-controlled study of 795 patients (30% men and 70% women) aged 20 to 94 (mean age of 63 years) treated with greater than or equal to 7.5 mg/day oral prednisone (or equivalent). A total of 384 patients were exposed to 5 mg oral daily bisphosphonate (active-control) and 394 patients were exposed to denosumab administered once every 6 months as a 60 mg subcutaneous dose. All patients were instructed to take at least 1000 mg of calcium and 800 IU of vitamin D supplementation per day.

The incidence of all-cause mortality was 0.5% (n = 2) in the active-control group and 1.5% (n = 6) in the denosumab group. The incidence of serious adverse events was 17% in the active-control group and 16% in the denosumab group. The percentage of patients who withdrew from the study due to adverse events was 3.6% and 3.8% for the active-control and denosumab groups, respectively.

Adverse reactions reported in ≥ 2% of patients with glucocorticoid-induced osteoporosis and more frequently with denosumab than in the active-control-treated patients are shown in the table below.

Table 2. Adverse Reactions Occurring in ≥ 2% of Patients with Glucocorticoid-induced Osteoporosis and More Frequently with Denosumab than in Active-Control-treated Patients

Preferred Term | Denosumab; (N = 394); n (%) | Oral Daily; Bisphosphonate; (Active-Control); (N = 384); n (%)
Back pain | 18 (4.6) | 17 (4.4)
Hypertension | 15 (3.8) | 13 (3.4)
Bronchitis | 15 (3.8) | 11 (2.9)
Headache | 14 (3.6) | 7 (1.8)
Dyspepsia | 12 (3.0) | 10 (2.6)
Urinary tract infection | 12 (3.0) | 8 (2.1)
Abdominal pain upper | 12 (3.0) | 7 (1.8)
Upper respiratory tract infection | 11 (2.8) | 10 (2.6)
Constipation | 11 (2.8) | 6 (1.6)
Vomiting | 10 (2.5) | 6 (1.6)
Dizziness | 9 (2.3) | 8 (2.1)
Fall | 8 (2.0) | 7 (1.8)
Polymyalgia rheumatica* | 8 (2.0) | 1 (0.3)

*Events of worsening of underlying polymyalgia rheumatica.

Osteonecrosis of the Jaw

No cases of ONJ were reported.

Atypical Subtrochanteric and Diaphyseal Femoral Fractures

Atypical femoral fractures were reported in 1 patient treated with denosumab. The duration of denosumab exposure to time of atypical femoral fracture diagnosis was at 8.0 months [see Warnings and Precautions (5.5)].

Serious Infections

Serious infection was reported in 15 patients (3.9%) in the active-control group and 17 patients (4.3%) in the denosumab group.

Dermatologic Adverse Reactions

Epidermal and dermal adverse events (such as dermatitis, eczema, and rashes) were reported in 16 patients (4.2%) in the active-control group and 15 patients (3.8%) in the denosumab group.

Treatment of Bone Loss in Patients Receiving Androgen Deprivation Therapy for Prostate Cancer or Adjuvant Aromatase Inhibitor Therapy for Breast Cancer

The safety of denosumab in the treatment of bone loss in men with nonmetastatic prostate cancer receiving androgen deprivation therapy (ADT) was assessed in a 3-year, randomized, double-blind, placebo-controlled, multinational study of 1468 men aged 48 to 97 years. A total of 725 men were exposed to placebo and 731 men were exposed to denosumab administered once every 6 months as a single 60 mg subcutaneous dose. All men were instructed to take at least 1000 mg of calcium and 400 IU of vitamin D supplementation per day.

The incidence of serious adverse events was 30.6% in the placebo group and 34.6% in the denosumab group. The percentage of patients who withdrew from the study due to adverse events was 6.1% and 7.0% for the placebo and denosumab groups, respectively.

The safety of denosumab in the treatment of bone loss in women with nonmetastatic breast cancer receiving aromatase inhibitor (AI) therapy was assessed in a 2-year, randomized, double-blind, placebo-controlled, multinational study of 252 postmenopausal women aged 35 to 84 years. A total of 120 women were exposed to placebo and 129 women were exposed to denosumab administered once every 6 months as a single 60 mg subcutaneous dose. All women were instructed to take at least 1000 mg of calcium and 400 IU of vitamin D supplementation per day.

The incidence of serious adverse events was 9.2% in the placebo group and 14.7% in the denosumab group. The percentage of patients who withdrew from the study due to adverse events was 4.2% and 0.8% for the placebo and denosumab groups, respectively.

Adverse reactions reported in ≥ 10% of denosumab-treated patients receiving ADT for prostate cancer or adjuvant AI therapy for breast cancer, and more frequently than in the placebo-treated patients were: arthralgia (13.0% placebo vs. 14.3% denosumab) and back pain (10.5% placebo vs. 11.5% denosumab). Pain in extremity (7.7% placebo vs. 9.9% denosumab) and musculoskeletal pain (3.8% placebo vs. 6.0% denosumab) have also been reported in clinical trials. Additionally, in denosumab-treated men with nonmetastatic prostate cancer receiving ADT, a greater incidence of cataracts was observed (1.2% placebo vs. 4.7% denosumab). Hypocalcemia (serum calcium < 8.4 mg/dL) was reported only in denosumab-treated patients (2.4% vs. 0.0%) at the month 1 visit.

6.2 Postmarketing Experience

Because postmarketing reactions are reported voluntarily from a population of uncertain size, it is not always possible to reliably estimate their frequency or establish a causal relationship to drug exposure.

The following adverse reactions have been identified during post-approval use of denosumab products:

- Drug-related hypersensitivity reactions: anaphylaxis, rash, urticaria, facial swelling, and erythema
- Hypocalcemia: severe symptomatic hypocalcemia resulting in hospitalization, life-threatening events, and fatal cases
- Musculoskeletal pain, including severe cases
- Parathyroid hormone (PTH): Marked elevation in serum PTH in patients with severe renal impairment (creatinine clearance < 30 mL/min) or receiving dialysis
- Multiple vertebral fractures following treatment discontinuation
- Cutaneous and mucosal lichenoid drug eruptions (e.g., lichen planus-like reactions)
- Alopecia
- Vasculitis (e.g., ANCA positive vasculitis, leukocytoclastic vasculitis)
- Drug reaction with eosinophilia and systemic symptoms (DRESS) syndrome

8 USE IN SPECIFIC POPULATIONS

8.1 Pregnancy

Risk Summary

Enoby is contraindicated for use in pregnant women because it may cause harm to a fetus. There are insufficient data with denosumab products use in pregnant women to inform any drug-associated risks for adverse developmental outcomes. In utero denosumab exposure from cynomolgus monkeys dosed monthly with denosumab throughout pregnancy at a dose 50-fold higher than the recommended human dose based on body weight resulted in increased fetal loss, stillbirths, and postnatal mortality, and absent lymph nodes, abnormal bone growth, and decreased neonatal growth [see Data].

Data

Animal Data

The effects of denosumab on prenatal development have been studied in both cynomolgus monkeys and genetically engineered mice in which RANK ligand (RANKL) expression was turned off by gene removal (a “knockout mouse”). In cynomolgus monkeys dosed subcutaneously with denosumab throughout pregnancy starting at gestational day 20 and at a pharmacologically active dose 50-fold higher than the recommended human dose based on body weight, there was increased fetal loss during gestation, stillbirths, and postnatal mortality. Other findings in offspring included absence of axillary, inguinal, mandibular, and mesenteric lymph nodes; abnormal bone growth, reduced bone strength, reduced hematopoiesis, dental dysplasia, and tooth malalignment; and decreased neonatal growth. At birth out to 1 month of age, infants had measurable blood levels of denosumab (22-621% of maternal levels).

Following a recovery period from birth out to 6 months of age, the effects on bone quality and strength returned to normal; there were no adverse effects on tooth eruption, though dental dysplasia was still apparent; axillary and inguinal lymph nodes remained absent, while mandibular and mesenteric lymph nodes were present, though small; and minimal to moderate mineralization in multiple tissues was seen in one recovery animal. There was no evidence of maternal harm prior to labor; adverse maternal effects occurred infrequently during labor. Maternal mammary gland development was normal. There was no fetal NOAEL (no observable adverse effect level) established for this study because only one dose of 50 mg/kg was evaluated. Mammary gland histopathology at 6 months of age was normal in female offspring exposed to denosumab in utero; however, development and lactation have not been fully evaluated.

In RANKL knockout mice, absence of RANKL (the target of denosumab) also caused fetal lymph node agenesis and led to postnatal impairment of dentition and bone growth. Pregnant RANKL knockout mice showed altered maturation of the maternal mammary gland, leading to impaired lactation [see Use in Specific Populations (8.2), Nonclinical Toxicology (13.2)].

The no effect dose for denosumab product-induced teratogenicity is unknown. However, a Cmax of 22.9 ng/mL was identified in cynomolgus monkeys as a level in which no biologic effects (NOEL) of denosumab were observed (no inhibition of RANKL) [see Clinical Pharmacology (12.3)].

8.2 Lactation

Risk Summary

There is no information regarding the presence of denosumab products in human milk, the effects on the breastfed infant, or the effects on milk production. Denosumab was detected in the maternal milk of cynomolgus monkeys up to 1 month after the last dose of denosumab (≤ 0.5% milk:serum ratio) and maternal mammary gland development was normal, with no impaired lactation. However, pregnant RANKL knockout mice showed altered maturation of the maternal mammary gland, leading to impaired lactation [see Use in Specific Populations (8.1), Nonclinical Toxicology (13.2)].

8.3 Females and Males of Reproductive Potential

Based on findings in animals, denosumab products can cause fetal harm when administered to a pregnant woman [see Use in Specific Populations (8.1)].

Pregnancy Testing

Verify the pregnancy status of females of reproductive potential prior to initiating Enoby treatment.

Contraception

Females

Advise females of reproductive potential to use effective contraception during therapy, and for at least 5 months after the last dose of Enoby.

Males

Denosumab was present at low concentrations (approximately 2% of serum exposure) in the seminal fluid of male subjects given denosumab. Following vaginal intercourse, the maximum amount of denosumab delivered to a female partner would result in exposures approximately 11000 times lower than the prescribed 60 mg subcutaneous dose, and at least 38 times lower than the NOEL in monkeys.

Therefore, male condom use would not be necessary as it is unlikely that a female partner or fetus would be exposed to pharmacologically relevant concentrations of denosumab products via seminal fluid [see Clinical Pharmacology (12.3)].

8.4 Pediatric Use

The safety and effectiveness of Enoby have not been established in pediatric patients.

In one multicenter, open-label study with denosumab conducted in 153 pediatric patients with osteogenesis imperfecta, aged 2 to 17 years, evaluating fracture risk reduction, efficacy was not demonstrated.

Hypercalcemia has been reported in pediatric patients with osteogenesis imperfecta treated with denosumab products. Some cases required hospitalization and were complicated by acute renal injury [see Warnings and Precautions (5.11)]. Clinical studies in pediatric patients with osteogenesis imperfecta were terminated early due to the occurrence of life-threatening events and hospitalizations due to hypercalcemia.

Safety and effectiveness were not demonstrated for the treatment of glucocorticoid-induced osteoporosis in one multicenter, randomized, double-blind, placebo-controlled, parallel-group study conducted in 24 pediatric patients with glucocorticoid-induced osteoporosis, aged 5 to 17 years, evaluating change from baseline in lumbar spine BMD Z-score.

Based on results from animal studies, denosumab may negatively affect long-bone growth and dentition in pediatric patients below the age of 4 years.

Juvenile Animal Toxicity Data

Treatment with denosumab products may impair long-bone growth in children with open growth plates and may inhibit eruption of dentition. In neonatal rats, inhibition of RANKL (the target of denosumab therapy) with a construct of osteoprotegerin bound to Fc (OPG-Fc) at doses ≤ 10 mg/kg was associated with inhibition of bone growth and tooth eruption. Adolescent primates treated with denosumab at doses 10 and 50 times (10 and 50 mg/kg dose) higher than the recommended human dose of 60 mg administered every 6 months, based on body weight (mg/kg), had abnormal growth plates, considered to be consistent with the pharmacological activity of denosumab [see Nonclinical Toxicology (13.2)].

Cynomolgus monkeys exposed in utero to denosumab exhibited bone abnormalities, an absence of axillary, inguinal, mandibular, and mesenteric lymph nodes, reduced hematopoiesis, tooth malalignment, and decreased neonatal growth. Some bone abnormalities recovered once exposure was ceased following birth; however, axillary and inguinal lymph nodes remained absent 6 months post-birth [see Use in Specific Populations (8.1)].

8.5 Geriatric Use

Of the total number of patients in clinical studies of denosumab, 9943 patients (76%) were ≥ 65 years old, while 3576 (27%) were ≥ 75 years old. Of the patients in the osteoporosis study in men, 133 patients (55%) were ≥ 65 years old, while 39 patients (16%) were ≥ 75 years old. Of the patients in the glucocorticoid-induced osteoporosis study, 355 patients (47%) were ≥ 65 years old, while 132 patients (17%) were ≥ 75 years old. No overall differences in safety or efficacy were observed between these patients and younger patients, and other reported clinical experience has not identified differences in responses between the elderly and younger patients, but greater sensitivity of some older individuals cannot be ruled out.

8.6 Renal Impairment

No dose adjustment is necessary in patients with renal impairment.

Severe hypocalcemia resulting in hospitalization, life-threatening events and fatal cases have been reported postmarketing. In clinical studies, patients with advanced chronic kidney disease (i.e., eGFR < 30 mL/min/1.73 m^2), including dialysis-dependent patients, were at greater risk of developing hypocalcemia. The presence of underlying chronic kidney disease-mineral bone disorder (CKD-MBD, renal osteodystrophy) markedly increases the risk of hypocalcemia. Concomitant use of calcimimetic drugs may also worsen hypocalcemia risk. Consider the benefits and risks to the patient when administering Enoby to patients with advanced chronic kidney disease. Monitor calcium and mineral levels (phosphorus and magnesium). Adequate intake of calcium and vitamin D is important in patients with advanced chronic kidney disease including dialysis-dependent patients [see Dosage and Administration (2.2), Warnings and Precautions (5.1), Adverse Reactions (6.1) and Clinical Pharmacology (12.3)].

11 DESCRIPTION

Denosumab-qbde is a human IgG2 monoclonal antibody with affinity and specificity for human RANKL (receptor activator of nuclear factor kappa-B ligand). Denosumab-qbde has an approximate molecular weight of 147 kDa and is produced in genetically engineered mammalian (Chinese hamster ovary) cells.

Enoby (denosumab-qbde) injection is a sterile, preservative-free, clear to slightly opalescent, colorless to pale yellow solution for subcutaneous use.

Each 1 mL single-dose prefilled syringe contains 60 mg denosumab-qbde (60 mg/mL solution), glacial acetic acid (1.0809 mg), polysorbate 20 (0.10 mg), sorbitol (46.0 mg), Water for Injection (USP). Sodium hydroxide may be added to adjust pH to approximately 5.2.

12 CLINICAL PHARMACOLOGY

12.1 Mechanism of Action

Denosumab products bind to RANKL, a transmembrane or soluble protein essential for the formation, function, and survival of osteoclasts, the cells responsible for bone resorption. Denosumab products prevent RANKL from activating its receptor, RANK, on the surface of osteoclasts and their precursors. Prevention of the RANKL/RANK interaction inhibits osteoclast formation, function, and survival, thereby decreasing bone resorption and increasing bone mass and strength in both cortical and trabecular bone.

12.2 Pharmacodynamics

In clinical studies, treatment with 60 mg of denosumab resulted in reduction in the bone resorption marker serum type 1 C-telopeptide (CTX) by approximately 85% by 3 days, with maximal reductions occurring by 1 month. CTX levels were below the limit of assay quantitation (0.049 ng/mL) in 39% to 68% of patients 1 to 3 months after dosing of denosumab. At the end of each dosing interval, CTX reductions were partially attenuated from a maximal reduction of ≥ 87% to ≥ 45% (range: 45% to 80%), as serum denosumab levels diminished, reflecting the reversibility of the effects of denosumab on bone remodeling. These effects were sustained with continued treatment. Upon reinitiation, the degree of inhibition of CTX by denosumab was similar to that observed in patients initiating denosumab treatment.

Consistent with the physiological coupling of bone formation and resorption in skeletal remodeling, subsequent reductions in bone formation markers (i.e., osteocalcin and procollagen type 1 N-terminal peptide [P1NP]) were observed starting 1 month after the first dose of denosumab. After discontinuation of denosumab therapy, markers of bone resorption increased to levels 40% to 60% above pretreatment values but returned to baseline levels within 12 months.

12.3 Pharmacokinetics

In a study conducted in healthy male and female volunteers (n = 73, age range: 18 to 64 years) following a single subcutaneously administered denosumab dose of 60 mg, the mean area-under-the-concentration-time curve up to 16 weeks (AUC0-16weeks) of denosumab was 316 mcg•day/mL (standard deviation [SD] = 101 mcg•day/mL). The mean maximum denosumab concentration (Cmax) was 6.75 mcg/mL (SD = 1.89 mcg/mL). No accumulation or change in denosumab pharmacokinetics with time is observed with multiple dosing of 60 mg subcutaneously administered once every 6 months.

Absorption

Following subcutaneous administration, the median time to maximum denosumab concentration (Tmax) was 10 days (range: 3 to 21 days).

Distribution

The mean volume of distribution for denosumab was 5.2 L (SD = 1.7 L).

Elimination

Serum denosumab concentrations declined over a period of 4 to 5 months with a mean half-life of 25.4 days (SD = 8.5 days; n = 46).

A population pharmacokinetic analysis was performed to evaluate the effects of demographic characteristics. This analysis showed no notable differences in pharmacokinetics with age (in postmenopausal women), race, or body weight (36 to 140 kg).

Seminal Fluid Pharmacokinetic Study

Serum and seminal fluid concentrations of denosumab were measured in 12 healthy male volunteers (age range: 43-65 years). After a single 60 mg subcutaneous administration of denosumab, the mean (± SD) Cmax values in the serum and seminal fluid samples were 6170 (± 2070) and 100 (± 81.9) ng/mL, respectively, resulting in a maximum seminal fluid concentration of approximately 2% of serum levels. The median (range) Tmax values in the serum and seminal fluid samples were 8.0 (7.9 to 21) and 21 (8.0 to 49) days, respectively. Among the subjects, the highest denosumab concentration in seminal fluid was 301 ng/mL at 22 days post-dose. On the first day of measurement (10 days post-dose), nine of eleven subjects had quantifiable concentrations in semen. On the last day of measurement (106 days post-dose), five subjects still had quantifiable concentrations of denosumab in seminal fluid, with a mean (± SD) seminal fluid concentration of 21.1 (± 36.5) ng/mL across all subjects (n = 12).

Drug Interactions

In a study of 19 postmenopausal women with low BMD and rheumatoid arthritis treated with etanercept (50 mg subcutaneous injection once weekly), a single-dose of denosumab (60 mg subcutaneous injection) was administered 7 days after the previous dose of etanercept. No clinically significant changes in the pharmacokinetics of etanercept were observed.

Cytochrome P450 substrates

In a study of 17 postmenopausal women with osteoporosis, midazolam (2 mg oral) was administered 2 weeks after a single-dose of denosumab (60 mg subcutaneous injection), which approximates the Tmax of denosumab. Denosumab did not affect the pharmacokinetics of midazolam, which is metabolized by cytochrome P450 3A4 (CYP3A4). This indicates that denosumab products should not alter the pharmacokinetics of drugs metabolized by CYP3A4 in postmenopausal women with osteoporosis.

Specific Populations

Gender: Mean serum denosumab concentration-time profiles observed in a study conducted in healthy men ≥ 50 years were similar to those observed in a study conducted in postmenopausal women using the same dose regimen.

Age: The pharmacokinetics of denosumab were not affected by age across all populations studied whose ages ranged from 28 to 87 years.

Race: The pharmacokinetics of denosumab were not affected by race.

Renal Impairment: In a study of 55 patients with varying degrees of renal function, including patients on dialysis, the degree of renal impairment had no effect on the pharmacokinetics of denosumab; thus, dose adjustment for renal impairment is not necessary.

Hepatic Impairment: No clinical studies have been conducted to evaluate the effect of hepatic impairment on the pharmacokinetics of denosumab products.

12.6 Immunogenicity

The observed incidence of anti-drug antibodies is highly dependent on the sensitivity and specificity of the assay. Differences in assay methods preclude meaningful comparisons of the incidence of anti-drug antibodies in the studies described below with the incidence of anti-drug antibodies in other studies, including those of denosumab or of other denosumab products.

Using an electrochemiluminescent bridging immunoassay, less than 1% (55 out of 8113) of patients treated with denosumab for up to 5 years tested positive for binding antibodies (including pre-existing, transient, and developing antibodies). None of the patients tested positive for neutralizing antibodies, as was assessed using a chemiluminescent cell-based in vitro biological assay.

There was no identified clinically significant effect of anti-drug antibodies on pharmacokinetics, pharmacodynamics, safety, or effectiveness of denosumab.

13 NONCLINICAL TOXICOLOGY

13.1 Carcinogenesis, Mutagenesis, Impairment of Fertility

Carcinogenicity

The carcinogenic potential of denosumab products has not been evaluated in long-term animal studies.

Mutagenicity

The genotoxic potential of denosumab products has not been evaluated.

Impairment of Fertility

Denosumab had no effect on female fertility or male reproductive organs in monkeys at doses that were 13- to 50-fold higher than the recommended human dose of 60 mg subcutaneously administered once every 6 months, based on body weight (mg/kg).

13.2 Animal Toxicology and/or Pharmacology

Denosumab products are inhibitors of osteoclastic bone resorption via inhibition of RANKL.

In ovariectomized monkeys, once-monthly treatment with denosumab suppressed bone turnover and increased BMD and strength of cancellous and cortical bone at doses 50-fold higher than the recommended human dose of 60 mg administered once every 6 months, based on body weight (mg/kg). Bone tissue was normal with no evidence of mineralization defects, accumulation of osteoid, or woven bone.

Because the biological activity of denosumab in animals is specific to nonhuman primates, evaluation of genetically engineered (“knockout”) mice or use of other biological inhibitors of the RANK/RANKL pathway, namely OPG-Fc, provided additional information on the pharmacodynamic properties of denosumab products. RANK/RANKL knockout mice exhibited absence of lymph node formation, as well as an absence of lactation due to inhibition of mammary gland maturation (lobulo-alveolar gland development during pregnancy). Neonatal RANK/RANKL knockout mice exhibited reduced bone growth and lack of tooth eruption. A corroborative study in 2-week-old rats given the RANKL inhibitor OPG-Fc also showed reduced bone growth, altered growth plates, and impaired tooth eruption. These changes were partially reversible in this model when dosing with the RANKL inhibitors was discontinued.

14 CLINICAL STUDIES

14.1 Treatment of Postmenopausal Women with Osteoporosis

The efficacy and safety of denosumab in the treatment of postmenopausal osteoporosis was demonstrated in a 3-year, randomized, double-blind, placebo-controlled trial. Enrolled women had a baseline BMD T-score between -2.5 and -4.0 at either the lumbar spine or total hip. Women with other diseases (such as rheumatoid arthritis, osteogenesis imperfecta, and Paget’s disease) or on therapies that affect bone were excluded from this study. The 7808 enrolled women were aged 60 to 91 years with a mean age of 72 years. Overall, the mean baseline lumbar spine BMD T-score was -2.8, and 23% of women had a vertebral fracture at baseline. Women were randomized to receive subcutaneous injections of either placebo (N = 3906) or denosumab 60 mg (N = 3902) once every 6 months. All women received at least 1000 mg calcium and 400 IU vitamin D supplementation daily.

The primary efficacy variable was the incidence of new morphometric (radiologically-diagnosed) vertebral fractures at 3 years. Vertebral fractures were diagnosed based on lateral spine radiographs (T4-L4) using a semiquantitative scoring method. Secondary efficacy variables included the incidence of hip fracture and nonvertebral fracture, assessed at 3 years.

Effect on Vertebral Fractures

Denosumab significantly reduced the incidence of new morphometric vertebral fractures at 1, 2, and 3 years (p < 0.0001), as shown in Table 3. The incidence of new vertebral fractures at year 3 was 7.2% in the placebo-treated women compared to 2.3% for the denosumab-treated women. The absolute risk reduction was 4.8% and relative risk reduction was 68% for new morphometric vertebral fractures at year 3.

Table 3. The Effect of Denosumab on the Incidence of New Vertebral Fractures in Postmenopausal Women

 | Proportion of Women with; Fracture (%)^+ |  | Absolute Risk; Reduction (%)*; (95% CI) | Relative Risk; Reduction (%)*; (95% CI)
 | Placebo; N = 3691; (%) | Denosumab; N = 3702; (%) | Absolute Risk; Reduction (%)*; (95% CI) | Relative Risk; Reduction (%)*; (95% CI)
0-1 Year | 2.2 | 0.9 | 1.4 (0.8, 1.9) | 61 (42, 74)
0-2 Years | 5.0 | 1.4 | 3.5 (2.7, 4.3) | 71 (61, 79)
0-3 Years | 7.2 | 2.3 | 4.8 (3.9, 5.8) | 68 (59, 74)

^+Event rates based on crude rates in each interval.

* Absolute risk reduction and relative risk reduction based on Mantel-Haenszel method adjusting for age group variable.

Denosumab was effective in reducing the risk for new morphometric vertebral fractures regardless of age, baseline rate of bone turnover, baseline BMD, baseline history of fracture, or prior use of a drug for osteoporosis.

Effect on Hip Fractures

The incidence of hip fracture was 1.2% for placebo-treated women compared to 0.7% for denosumab-treated women at year 3. The age-adjusted absolute risk reduction of hip fractures was 0.3% with a relative risk reduction of 40% at 3 years (p = 0.04) (see Figure 1).

Figure 1. Cumulative Incidence of Hip Fractures Over 3 Years

Effect on Nonvertebral Fractures

Treatment with denosumab resulted in a significant reduction in the incidence of nonvertebral fractures (see Table 4).

Table 4. The Effect of Denosumab on the Incidence of Nonvertebral Fractures at Year 3

 | Proportion of Women with; Fracture (%)^+ |  | Absolute Risk; Reduction (%); (95% CI) | Relative Risk; Reduction (%); (95% CI)
 | Placebo; N = 3906; (%) | Denosumab; N = 3902; (%) | Absolute Risk; Reduction (%); (95% CI) | Relative Risk; Reduction (%); (95% CI)
Nonvertebral fracture^1 | 8.0 | 6.5 | 1.5 (0.3, 2.7) | 20 (5, 33)*

^+Event rates based on Kaplan-Meier estimates at 3 years.

^1 Excluding those of the vertebrae (cervical, thoracic, and lumbar), skull, facial, mandible, metacarpus, and finger and toe phalanges.

* p-value = 0.01.

Effect on Bone Mineral Density (BMD)

Treatment with denosumab significantly increased BMD at all anatomic sites measured at 3 years. The treatment differences in BMD at 3 years were 8.8% at the lumbar spine, 6.4% at the total hip, and 5.2% at the femoral neck. Consistent effects on BMD were observed at the lumbar spine, regardless of baseline age, race, weight/body mass index (BMI), baseline BMD, and level of bone turnover.

After denosumab discontinuation, BMD returned to approximately baseline levels within 12 months.

Bone Histology and Histomorphometry

A total of 115 transiliac crest bone biopsy specimens were obtained from 92 postmenopausal women with osteoporosis at either month 24 and/or month 36 (53 specimens in denosumab group, 62 specimens in placebo group). Of the biopsies obtained, 115 (100%) were adequate for qualitative histology and 7 (6%) were adequate for full quantitative histomorphometry assessment.

Qualitative histology assessments showed normal architecture and quality with no evidence of mineralization defects, woven bone, or marrow fibrosis in patients treated with denosumab.

The presence of double tetracycline labeling in a biopsy specimen provides an indication of active bone remodeling, while the absence of tetracycline label suggests suppressed bone formation. In patients treated with denosumab, 35% had no tetracycline label present at the month 24 biopsy and 38% had no tetracycline label present at the month 36 biopsy, while 100% of placebo-treated patients had double label present at both time points. When compared to placebo, treatment with denosumab resulted in virtually absent activation frequency and markedly reduced bone formation rates. However, the long-term consequences of this degree of suppression of bone remodeling are unknown.

14.2 Treatment to Increase Bone Mass in Men with Osteoporosis

The efficacy and safety of denosumab in the treatment to increase bone mass in men with osteoporosis was demonstrated in a 1-year, randomized, double-blind, placebo-controlled trial. Enrolled men had a baseline BMD T-score between -2.0 and -3.5 at the lumbar spine or femoral neck. Men with a BMD T-score between -1.0 and -3.5 at the lumbar spine or femoral neck were also enrolled if there was a history of prior fragility fracture. Men with other diseases (such as rheumatoid arthritis, osteogenesis imperfecta, and Paget’s disease) or on therapies that may affect bone were excluded from this study. The 242 men enrolled in the study ranged in age from 31 to 84 years with a mean age of 65 years. Men were randomized to receive SC injections of either placebo (n = 121) or denosumab 60 mg (n = 121) once every 6 months. All men received at least 1000 mg calcium and at least 800 IU vitamin D supplementation daily.

Effect on Bone Mineral Density (BMD)

The primary efficacy variable was percent change in lumbar spine BMD from baseline to 1-year. Secondary efficacy variables included percent change in total hip, and femoral neck BMD from baseline to 1-year.

Treatment with denosumab significantly increased BMD at 1-year. The treatment differences in BMD at 1-year were 4.8% (+0.9% placebo, +5.7% denosumab; (95% CI: 4.0, 5.6); p < 0.0001) at the lumbar spine, 2.0% (+0.3% placebo, +2.4% denosumab) at the total hip, and 2.2% (0.0% placebo, +2.1% denosumab) at femoral neck. Consistent effects on BMD were observed at the lumbar spine regardless of baseline age, race, BMD, testosterone concentrations, and level of bone turnover.

Bone Histology and Histomorphometry

A total of 29 transiliac crest bone biopsy specimens were obtained from men with osteoporosis at 12 months (17 specimens in denosumab group, 12 specimens in placebo group). Of the biopsies obtained, 29 (100%) were adequate for qualitative histology and, in denosumab patients, 6 (35%) were adequate for full quantitative histomorphometry assessment. Qualitative histology assessments showed normal architecture and quality with no evidence of mineralization defects, woven bone, or marrow fibrosis in patients treated with denosumab. The presence of double tetracycline labeling in a biopsy specimen provides an indication of active bone remodeling, while the absence of tetracycline label suggests suppressed bone formation. In patients treated with denosumab, 6% had no tetracycline label present at the month 12 biopsy, while 100% of placebo-treated patients had double label present. When compared to placebo, treatment with denosumab resulted in markedly reduced bone formation rates. However, the long-term consequences of this degree of suppression of bone remodeling are unknown.

14.3 Treatment of Glucocorticoid-Induced Osteoporosis

The efficacy and safety of denosumab in the treatment of patients with glucocorticoid-induced osteoporosis was assessed in the 12-month primary analysis of a 2-year, randomized, multicenter, double-blind, parallel-group, active-controlled study (NCT 01575873) of 795 patients (70% women and 30% men) aged 20 to 94 years (mean age of 63 years) treated with greater than or equal to 7.5 mg/day oral prednisone (or equivalent) for < 3 months prior to study enrollment and planning to continue treatment for a total of at least 6 months (glucocorticoid-initiating subpopulation; n = 290) or ≥ 3 months prior to study enrollment and planning to continue treatment for a total of at least 6 months (glucocorticoid-continuing subpopulation, n = 505). Enrolled patients < 50 years of age were required to have a history of osteoporotic fracture. Enrolled patients ≥ 50 years of age who were in the glucocorticoid-continuing subpopulation were required to have a baseline BMD T-score of ≤ -2.0 at the lumbar spine, total hip, or femoral neck; or a BMD T-score ≤ -1.0 at the lumbar spine, total hip, or femoral neck and a history of osteoporotic fracture.

Patients were randomized (1:1) to receive either an oral daily bisphosphonate (active-control, risedronate 5 mg once daily) (n = 397) or denosumab 60 mg subcutaneously once every 6 months (n = 398) for one year. Randomization was stratified by gender within each subpopulation. Patients received at least 1000 mg calcium and 800 IU vitamin D supplementation daily.

Effect on Bone Mineral Density (BMD)

In the glucocorticoid-initiating subpopulation, denosumab significantly increased lumbar spine BMD compared to the active-control at one year (Active-control 0.8%, denosumab 3.8%) with a treatment difference of 2.9% (p < 0.001). In the glucocorticoid-continuing subpopulation, denosumab significantly increased lumbar spine BMD compared to active-control at one year (Active-control 2.3%, denosumab 4.4%) with a treatment difference of 2.2% (p < 0.001). Consistent effects on lumbar spine BMD were observed regardless of gender; race; geographic region; menopausal status; and baseline age, lumbar spine BMD T-score, and glucocorticoid dose within each subpopulation.

Bone Histology

Bone biopsy specimens were obtained from 17 patients (11 in the active-control treatment group and 6 in the denosumab treatment group) at Month 12. Of the biopsies obtained, 17 (100%) were adequate for qualitative histology. Qualitative assessments showed bone of normal architecture and quality without mineralization defects or bone marrow abnormality. The presence of double tetracycline labeling in a biopsy specimen provides an indication of active bone remodeling, while the absence of tetracycline label suggests suppressed bone formation. In patients treated with active-control, 100% of biopsies had tetracycline label. In patients treated with denosumab, 1 (33%) had tetracycline label and 2 (67%) had no tetracycline label present at the 12-month biopsy. Evaluation of full quantitative histomorphometry including bone remodeling rates was not possible in the glucocorticoid-induced osteoporosis population treated with denosumab. The long-term consequences of this degree of suppression of bone remodeling in glucocorticoid-treated patients is unknown.

14.4 Treatment of Bone Loss in Men with Prostate Cancer

The efficacy and safety of denosumab in the treatment of bone loss in men with nonmetastatic prostate cancer receiving androgen deprivation therapy (ADT) were demonstrated in a 3-year, randomized (1:1), double-blind, placebo-controlled, multinational study. Men less than 70 years of age had either a BMD T-score at the lumbar spine, total hip, or femoral neck between -1.0 and -4.0, or a history of an osteoporotic fracture. The mean baseline lumbar spine BMD T-score was -0.4, and 22% of men had a vertebral fracture at baseline. The 1468 men enrolled ranged in age from 48 to 97 years (median 76 years). Men were randomized to receive subcutaneous injections of either placebo (n = 734) or denosumab 60 mg (n = 734) once every 6 months for a total of 6 doses. Randomization was stratified by age (< 70 years vs. ≥ 70 years) and duration of ADT at trial entry (≤ 6 months vs. > 6 months). Seventy-nine percent of patients received ADT for more than 6 months at study entry. All men received at least 1000 mg calcium and 400 IU vitamin D supplementation daily.

Effect on Bone Mineral Density (BMD)

The primary efficacy variable was percent change in lumbar spine BMD from baseline to month 24. An additional key secondary efficacy variable was the incidence of new vertebral fracture through month 36 diagnosed based on x-ray evaluation by two independent radiologists. Lumbar spine BMD was higher at 2 years in denosumab-treated patients as compared to placebo-treated patients [-1.0% placebo, +5.6% denosumab; treatment difference 6.7% (95% CI: 6.2, 7.1); p < 0.0001].

With approximately 62% of patients followed for 3 years, treatment differences in BMD at 3 years were 7.9% (-1.2% placebo, +6.8% denosumab) at the lumbar spine, 5.7% (-2.6% placebo, +3.2% denosumab) at the total hip, and 4.9% (-1.8% placebo, +3.0% denosumab) at the femoral neck. Consistent effects on BMD were observed at the lumbar spine in relevant subgroups defined by baseline age, BMD, and baseline history of vertebral fracture.

Effect on Vertebral Fractures

Denosumab significantly reduced the incidence of new vertebral fractures at 3 years (p = 0.0125), as shown in Table 5.

Table 5. The Effect of Denosumab on the Incidence of New Vertebral Fractures in Men with Nonmetastatic Prostate Cancer

 | Proportion of Men with Fracture; (%)^+ |  | Absolute Risk; Reduction (%)*; (95% CI) | Relative Risk; Reduction (%)*; (95% CI)
 | Placebo; N = 673; (%) | Denosumab; N = 679; (%) | Absolute Risk; Reduction (%)*; (95% CI) | Relative Risk; Reduction (%)*; (95% CI)
0-1 Year | 1.9 | 0.3 | 1.6 (0.5, 2.8) | 85 (33, 97)
0-2 Years | 3.3 | 1.0 | 2.2 (0.7, 3.8) | 69 (27, 86)
0-3 Years | 3.9 | 1.5 | 2.4 (0.7, 4.1) | 62 (22, 81)

^+Event rates based on crude rates in each interval.

* Absolute risk reduction and relative risk reduction based on Mantel-Haenszel method adjusting for age group and ADT duration variables.

14.5 Treatment of Bone Loss in Women with Breast Cancer

The efficacy and safety of denosumab in the treatment of bone loss in women receiving adjuvant aromatase inhibitor (AI) therapy for breast cancer was assessed in a 2-year, randomized (1:1), double-blind, placebo-controlled, multinational study. Women had baseline BMD T-scores between -1.0 to -2.5 at the lumbar spine, total hip, or femoral neck, and had not experienced fracture after age 25. The mean baseline lumbar spine BMD T-score was -1.1, and 2.0% of women had a vertebral fracture at baseline. The 252 women enrolled ranged in age from 35 to 84 years (median 59 years). Women were randomized to receive subcutaneous injections of either placebo (n = 125) or denosumab 60 mg (n = 127) once every 6 months for a total of 4 doses. Randomization was stratified by duration of adjuvant AI therapy at trial entry (≤ 6 months vs. > 6 months). Sixty-two percent of patients received adjuvant AI therapy for more than 6 months at study entry. All women received at least 1000 mg calcium and 400 IU vitamin D supplementation daily.

Effect on Bone Mineral Density (BMD)

The primary efficacy variable was percent change in lumbar spine BMD from baseline to month 12. Lumbar spine BMD was higher at 12 months in denosumab-treated patients as compared to placebo-treated patients [-0.7% placebo, +4.8% denosumab; treatment difference 5.5% (95% CI: 4.8, 6.3); p < 0.0001].

With approximately 81% of patients followed for 2 years, treatment differences in BMD at 2 years were 7.6% (-1.4% placebo, +6.2% denosumab) at the lumbar spine, 4.7% (-1.0% placebo, +3.8% denosumab) at the total hip, and 3.6% (-0.8% placebo, +2.8% denosumab) at the femoral neck.

16 HOW SUPPLIED/STORAGE AND HANDLING

How Supplied

Enoby (denosumab-qbde) injection is a clear to slightly opalescent, colorless to pale yellow solution supplied in a single-dose prefilled syringe with a safety guard. The prefilled syringe is not made with natural rubber latex.

60 mg/mL in a single-dose prefilled syringe | 1 per carton | NDC 0143-9165-01

Storage and Handling

Store Enoby refrigerated at 2°C to 8°C (36°F to 46°F) in the original carton to protect from light. Do not freeze. Prior to administration, Enoby may be allowed to reach room temperature up to 25°C (77°F) in the original container. Once removed from the refrigerator, Enoby must not be exposed to temperatures above 25°C (77°F) and must be used within 30 days. Discard Enoby if not used within the 30 days. Do not use Enoby after the expiry date printed on the label.

Protect Enoby from direct light and heat.

Avoid vigorous shaking of Enoby.

17 PATIENT COUNSELING INFORMATION

Advise the patient to read the FDA-approved patient labeling (Medication Guide).

Hypocalcemia

Advise the patient to adequately supplement with calcium and vitamin D and instruct them on the importance of maintaining serum calcium levels while receiving Enoby [see Warnings and Precautions (5.1), Use in Specific Populations (8.6)]. Advise patients to seek prompt medical attention if they develop signs or symptoms of hypocalcemia.

Severe Hypocalcemia in Patients with Advanced Chronic Kidney Disease

Advise patients with advanced chronic kidney disease, including those who are dialysis-dependent, about the symptoms of hypocalcemia and the importance of maintaining serum calcium levels with adequate calcium and activated vitamin D supplementation. Advise these patients to have their serum calcium measured weekly for the first month after Enoby administration and monthly thereafter [see Dosage and Administration (2.2), Warnings and Precautions (5.1), Use in Specific Populations (8.6)].

Drug Products with Same Active Ingredient

Advise patients that if they receive Enoby, they should not receive other denosumab products concomitantly [see Warnings and Precautions (5.2)].

Hypersensitivity

Advise patients to seek prompt medical attention if signs or symptoms of hypersensitivity reactions occur. Advise patients who have had signs or symptoms of systemic hypersensitivity reactions that they should not receive denosumab products [see Warnings and Precautions (5.3), Contraindications (4)].

Osteonecrosis of the Jaw

Advise patients to maintain good oral hygiene during treatment with Enoby and to inform their dentist prior to dental procedures that they are receiving Enoby. Patients should inform their physician or dentist if they experience persistent pain and/or slow healing of the mouth or jaw after dental surgery [see Warnings and Precautions (5.4)].

Atypical Subtrochanteric and Diaphyseal Femoral Fractures

Advise patients to report new or unusual thigh, hip, or groin pain [see Warnings and Precautions (5.5)].

Multiple Vertebral Fractures (MVF) Following Treatment Discontinuation

Advise patients not to interrupt Enoby therapy without talking to their physician [see Warnings and Precautions (5.6)].

Serious Infections

Advise patients to seek prompt medical attention if they develop signs or symptoms of infections, including cellulitis [see Warnings and Precautions (5.7)].

Dermatologic Adverse Reactions

Advise patients to seek prompt medical attention if they develop signs or symptoms of dermatological reactions (such as dermatitis, rashes, and eczema) [see Warnings and Precautions (5.8)].

Musculoskeletal Pain

Inform patients that severe bone, joint, and/or muscle pain have been reported in patients taking denosumab products. Patients should report severe symptoms if they develop [see Warnings and Precautions (5.9)].

Pregnancy/Nursing

Counsel females of reproductive potential to use effective contraceptive measure to prevent pregnancy during treatment and for at least 5 months after the last dose of Enoby. Advise the patient to contact their physician immediately if pregnancy does occur during these times. Advise patients not to take Enoby while pregnant or breastfeeding. If a patient wishes to start breastfeeding after treatment, advise her to discuss the appropriate timing with her physician [see Contraindications (4), Use in Specific Populations (8.1)].

Schedule of Administration

Advise patients that if a dose of Enoby is missed, the injection should be administered as soon as convenient. Thereafter, schedule injections every 6 months from the date of the last injection.

Enoby™ (denosumab-qbde)

Manufactured by:

Hikma Pharmaceuticals USA Inc.

2 Esterbrook Lane

Cherry Hill, NJ 08003 USA

U.S. License No. 2356

Product of Hungary

Prolia® is a registered trademark of Amgen Inc.

MEDICATION GUIDE

Enoby™ (eh-noé-bee)

(denosumab-qbde)

Injection, for subcutaneous use

What is the most important information I should know about Enoby?

If you receive Enoby, you should not receive other denosumab products at the same time.

Enoby can cause serious side effects including:

- Increased risk of severe low calcium levels in your blood (hypocalcemia). Enoby may lower the calcium levels in your blood. If you have low blood calcium before you start receiving Enoby, it may get worse during treatment. Your low blood calcium must be treated before you receive Enoby. Talk to your doctor before starting Enoby. Your doctor may prescribe calcium and vitamin D to help prevent low calcium levels in your blood while you take Enoby. Take calcium and vitamin D as your doctor tells you to.

If you have advanced chronic kidney disease (may or may not be on kidney dialysis), Enoby may increase your risk for severe low calcium levels in your blood, which could result in hospitalization, life-threatening events and death. A mineral and bone disorder associated with kidney disease called chronic kidney disease-mineral bone disorder (CKD-MBD) may increase your risk for severe low calcium levels in blood. Before you start Enoby and during treatment, your doctor may need to do certain blood tests to check for CKD-MBD.

Most people with low blood calcium levels do not have symptoms, but some people may have symptoms. Call your doctor right away if you have symptoms of low blood calcium such as:

- spasms, twitches, or cramps in your muscles
- numbness or tingling in your fingers, toes, or around your mouth

- Serious allergic reactions. Serious allergic reactions have happened in people who take denosumab products. Call your doctor or go to your nearest emergency room right away if you have any symptoms of a serious allergic reaction. Symptoms of a serious allergic reaction may include:

- low blood pressure (hypotension)
- trouble breathing
- throat tightness
- swelling of your face, lips, or tongue
- rash
- itching
- hives

- Severe jaw bone problems (osteonecrosis). Severe jaw bone problems may happen when you take Enoby. Your doctor should examine your mouth before you start Enoby. Your doctor may tell you to see your dentist before you start Enoby. It is important for you to practice good mouth care during treatment with Enoby. Ask your doctor or dentist about good mouth care if you have any questions.
- Unusual thigh bone fractures. Some people have developed unusual fractures in their thigh bone. Symptoms of a fracture include new or unusual pain in your hip, groin, or thigh.
- Increased risk of broken bones, including broken bones in the spine, after stopping, skipping or delaying Enoby. Talk with your doctor before starting Enoby treatment. After your treatment with Enoby is stopped, or if you skip or delay taking a dose, your risk for breaking bones, including bones in your spine, is increased. Your risk for having more than 1 broken bone in your spine is increased if you have already had a broken bone in your spine. Do not stop, skip or delay taking Enoby without first talking with your doctor. If your Enoby treatment is stopped, talk to your doctor about other medicine that you can take.
- Serious infections. Serious infections in your skin, lower stomach area (abdomen), bladder, or ear may happen if you take Enoby. Inflammation of the inner lining of the heart (endocarditis) due to an infection also may happen more often in people who take Enoby. You may need to go to the hospital for treatment if you develop an infection.

Enoby is a medicine that may affect the ability of your body to fight infections. People who have a weakened immune system or take medicines that affect the immune system may have an increased risk for developing serious infections. Call your doctor right away if you have any of the following symptoms of infection:

- fever or chills
- skin that looks red or swollen and is hot or tender to touch
- fever, shortness of breath, cough that will not go away
- severe abdominal pain
- frequent or urgent need to urinate or burning feeling when you urinate

- Skin problems. Skin problems such as inflammation of your skin (dermatitis), rash, and eczema may happen if you take Enoby. Call your doctor if you have any of the following symptoms of skin problems that do not go away or get worse:

- redness
- itching
- small bumps or patches (rash)
- your skin is dry or feels like leather
- blisters that ooze or become crusty
- skin peeling

- Bone, joint, or muscle pain. Some people who take denosumab products develop severe bone, joint, or muscle pain.

Call your doctor right away if you have any of these side effects.

What is Enoby?

Enoby is a prescription medicine used to:

- Treat osteoporosis (thinning and weakening of bone) in women after menopause (“change of life”) who:
  - are at high risk for fracture (broken bone)
  - cannot use another osteoporosis medicine or other osteoporosis medicines did not work well
- Increase bone mass in men with osteoporosis who are at high risk for fracture.
- Treat osteoporosis in men and women who will be taking corticosteroid medicines (such as prednisone) for at least 6 months and are at high risk for fracture.
- Treat bone loss in men who are at high risk for fracture receiving certain treatments for prostate cancer that has not spread to other parts of the body.
- Treat bone loss in women who are at high risk for fracture receiving certain treatments for breast cancer that has not spread to other parts of the body.

It is not known if Enoby is safe and effective in children. Enoby is not approved for use in children.

Do not take Enoby if you:

- have been told by your doctor that your blood calcium level is too low.
- are pregnant or plan to become pregnant.

- are allergic to denosumab products or any of the ingredients in Enoby. See the end of this Medication Guide for a complete list of ingredients in Enoby.

Before taking Enoby, tell your doctor about all of your medical conditions, including if you:

- are taking other denosumab products.
- have low blood calcium.
- cannot take daily calcium and vitamin D.
- had parathyroid or thyroid surgery (glands located in your neck).
- have been told you have trouble absorbing minerals in your stomach or intestines (malabsorption syndrome).
- have kidney problems or are on kidney dialysis.
- are taking medicine that can lower your blood calcium levels.
- plan to have dental surgery or teeth removed.
- are pregnant or plan to become pregnant. Enoby may harm your unborn baby.
  Females who are able to become pregnant:
  - Your healthcare provider should do a pregnancy test before you start treatment with Enoby.
  - You should use an effective method of birth control (contraception) during treatment with Enoby and for at least 5 months after your last dose of Enoby.
  - Tell your doctor right away if you become pregnant while taking Enoby.
- are breastfeeding or plan to breastfeed. It is not known if Enoby passes into your breast milk. You and your doctor should decide if you will take Enoby or breastfeed. You should not do both.

Tell your doctor about all the medicines you take, including prescription and over-the-counter medicines, vitamins, and herbal supplements.

Know the medicines you take. Keep a list of medicines with you to show to your doctor or pharmacist when you get a new medicine.

How will I receive Enoby?

- Enoby is an injection that will be given to you by a healthcare provider. Enoby is injected under your skin (subcutaneous).
- You will receive Enoby 1 time every 6 months.
- You should take calcium and vitamin D as your doctor tells you to while you receive Enoby.
- If you miss a dose of Enoby, you should receive your injection as soon as you can.
- Take good care of your teeth and gums while you receive Enoby. Brush and floss your teeth regularly.
- Tell your dentist that you are receiving Enoby before you have dental work.

What are the possible side effects of Enoby?

Enoby may cause serious side effects.

- See “What is the most important information I should know about Enoby?”
- It is not known if the use of Enoby over a long period of time may cause slow healing of broken bones.
  The most common side effects of Enoby in women who are being treated for osteoporosis after menopause are:
  - back pain
  - pain in your arms and legs
  - high cholesterol
  - muscle pain
  - bladder infection
  The most common side effects of Enoby in men with osteoporosis are:
  - back pain
  - joint pain
  - common cold (runny nose or sore throat)
  The most common side effects of Enoby in patients with glucocorticoid-induced osteoporosis are:
  - back pain
  - high blood pressure
  - lung infection (bronchitis)
  - headache

The most common side effects of Enoby in patients receiving certain treatments for prostate or breast cancer are:

- joint pain
- back pain
- pain in your arms and legs
- muscle pain

Tell your doctor if you have any side effect that bothers you or that does not go away.

These are not all the possible side effects of Enoby.

Call your doctor for medical advice about side effects. You may report side effects to FDA at 1-800-FDA-1088.

How should I store Enoby if I need to pick it up from a pharmacy?

- Keep Enoby in a refrigerator at 36°F to 46°F (2°C to 8°C) in the original carton.
- Do not freeze Enoby.
- When you remove Enoby from the refrigerator, Enoby must be kept at room temperature [up to 77°F (25°C)] in the original carton and must be used within 30 days.
- Do not keep Enoby at temperatures above 77°F (25°C). Warm temperatures will affect how Enoby works.
- Do not shake Enoby.
- Keep Enoby in the original carton to protect from light.

Keep Enoby and all medicines out of the reach of children.

General information about the safe and effective use of Enoby.

Medicines are sometimes prescribed for purposes other than those listed in a Medication Guide. Do not use Enoby for a condition for which it was not prescribed. Do not give Enoby to other people, even if they have the same symptoms that you have. It may harm them. You can ask your doctor or pharmacist for information about Enoby that is written for healthcare providers.

What are the ingredients in Enoby?

Active ingredient: denosumab-qbde

Inactive ingredients: glacial acetic acid, polysorbate 20, sorbitol, Water for Injection (USP), and sodium hydroxide is added to adjust pH.

Manufactured by:

Hikma Pharmaceuticals USA Inc.

2 Esterbrook Lane

Cherry Hill, NJ 08003 USA

U.S. License No. 2356

Product of Hungary

For more information, go to www.enobyinfo.com or call Hikma Pharmaceuticals USA Inc. at 1-877-845-0689.

This Medication Guide has been approved by the U.S. Food and Drug Administration. Issued: 09/2025

PRINCIPAL DISPLAY PANEL

NDC 0143-9165-01

Enoby™ (denosumab-qbde) injection

60 mg/mL

For Subcutaneous Use Only

Single-Dose Prefilled Syringe.

Discard unused portion.

Hikma Pharmaceuticals USA Inc.

U.S. License No. 2356 Rx only

NDC 0143-9165-01 Rx only

Enoby™ (denosumab-qbde)

Injection

60 mg/mL

For Subcutaneous Use Only.

Sterile-Solution - No Preservative.

One 60 mg/mL Single-Dose Prefilled Syringe. Discard unused portion.